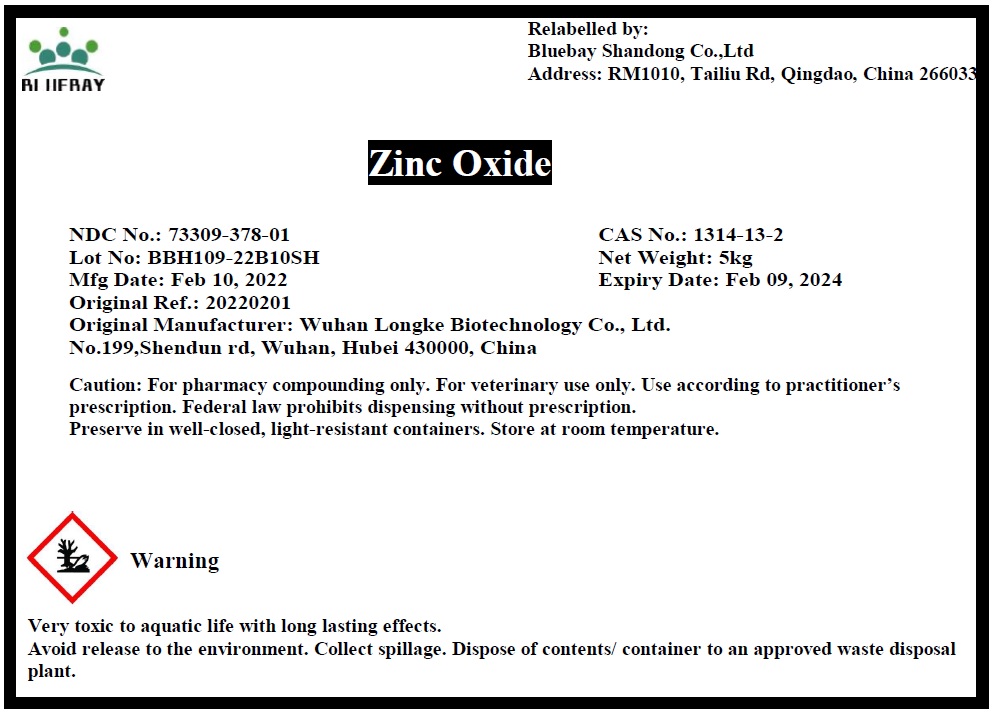 DRUG LABEL: Zinc Oxide
NDC: 73309-378 | Form: POWDER
Manufacturer: BLUEBAY SHANDONG CO.,LTD
Category: other | Type: BULK INGREDIENT - ANIMAL DRUG
Date: 20220317

ACTIVE INGREDIENTS: ZINC OXIDE 1 kg/1 kg

Zinc Oxide